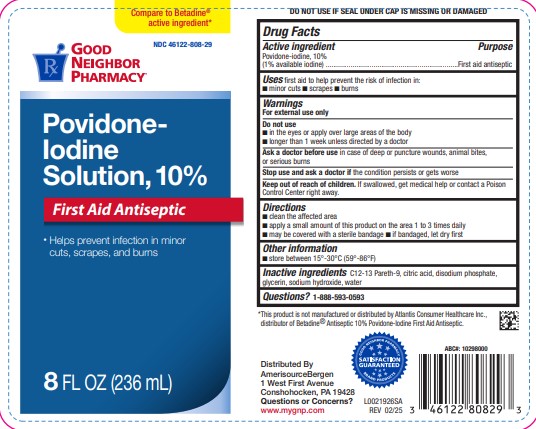 DRUG LABEL: First Aid Antiseptic
NDC: 46122-808 | Form: SOLUTION
Manufacturer: Amerisource Bergen
Category: otc | Type: HUMAN OTC DRUG LABEL
Date: 20260129

ACTIVE INGREDIENTS: POVIDONE-IODINE 10 mg/100 mL
INACTIVE INGREDIENTS: SODIUM PHOSPHATE, DIBASIC, ANHYDROUS; C12-13 PARETH-9; WATER; CITRIC ACID MONOHYDRATE; GLYCERIN; SODIUM HYDROXIDE

Good Neighbor Pharmacy 050.002/050AE
Povidone-Iodine Solution, 10%

Tamper Evident Statement

DO NOT USE IF SEAL UNDER CAP IS MISSING OR DAMAGED

Active Ingredient

Povidone-iodine, 10% (1% available iodine)

Purpose

First aid antiseptic

Uses

first aid to help prevent the risk of infection in:

- minor cuts
- scrapes
- burns

Warnings

For external use only

Do not use

- in the eyes or apply over large areas of the body
- longer than 1 week unless directed by a doctor

Ask a doctor before use

in case of deep or puncture wounds, animal bites, or serious burns

Stop use and ask a doctor if

condition persists or gets worse

Keep out of reach of children.

If swallowed, get medical help or contact a Poison Control Center right away.

Directions

- clean the affected area
- apply a small amount of this product on the area 1 to 3 times daily
- may be covered with a sterile bandage
- if bandaged, let dry first

Other information

- store between 15º-30ºC (59º-86ºF)

Inactive ingredients

C12-13 Pareth-9, citric acid, disodium phosphate, glycerin, sodium hydroxide, water

Questions?

1-888-593-0593

Disclaimer

*This product is not manufactured or distributed by Atlantis Consumer Healthcare Inc., distributor of BetadineAntiseptic 10% Povidone-Iodine First Aid Antiseptic.

ADVERSE REACTION

Distributed By

AmerisourceBergen

1 West First Avenue

Conshohocken, PA 19428

Questions or Concerns?

www.mygnp.com

SATISFACTION GUARANTEED

GOOD NEIGHBOR PHARMACY BRAND PRODUCTS

PRINCIPAL DISPLAY PANEL

Compare to Betadine®active ingredient*

NDC 46122-808-29

GOOD NEIGHBOR PHARMACY ®

Povidone-Iodine Solution, 10%

First Aid Antiseptic

- Helps prevent infection in minor cuts, scrapes, and burns

8 FL OZ (236 mL)